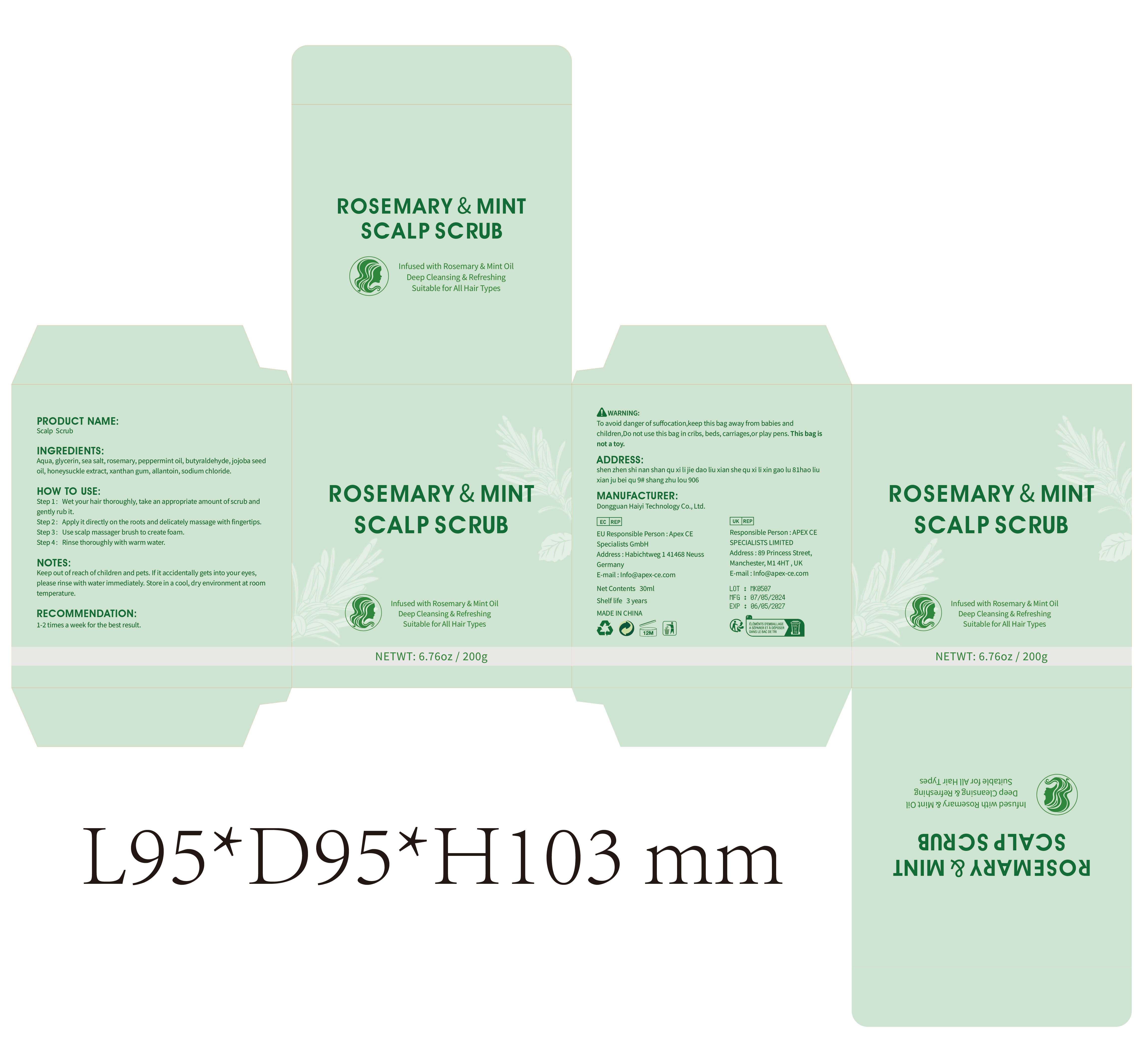 DRUG LABEL: Scalp Scrub
NDC: 84732-018 | Form: CREAM
Manufacturer: Dongguan Haiyi Technology Co.,Ltd.
Category: otc | Type: HUMAN OTC DRUG LABEL
Date: 20240926

ACTIVE INGREDIENTS: WATER 1 mg/200 g
INACTIVE INGREDIENTS: GLYCERIN; SEA SALT; SODIUM CHLORIDE; PEPPERMINT OIL; JOJOBA OIL; ROSEMARY; HONEY; BUTYRALDEHYDE; XANTHAN GUM; ALLANTOIN

Active ingredient

Aqua

Inactive ingredient

glycerin, sea salt, rosemary, peppermint oil, butyraldehyde, jojoba seedoil, honeysuckle extract, xanthan gum, allantoin, sodium chloride.

Purpose section

Infused with Rosemary & Mint Oil Deep Cleansing& RefreshingSuitable for All Hair Types

HOW TO USE

Step 1: Wet your hair thoroughly, take an appropriate amount ofscrub andgently rub it.
Step 2: Applyit directly on the roots and delicately massage with fingertips.
Step 3: Use scalp massager brush to create foam.
Step 4: Rinse thoroughly with warm water.

NOTES:

Keep out of reach ofchildren and pets, lf it accidentally gets into your eyes,please rinse with waterimmediately, Store in a cool, dry environment at roomtemperature.

RECOMMENDATION

1-2 times a week for the best result.

stop use

This product may cause allergic reactions in asmall number of people.
lf youexperience any discomfort,please stop using it immediately.

OUT OF CHILDREN

KEEP THE PRODUCT OUT OF REACH OF CHILDREN to

WARNING

To avoid danger of suffocation,keep this bag away from babies and children,Do not use this bag in cribs, beds, carriages,or play pens. This bag is not a toy.